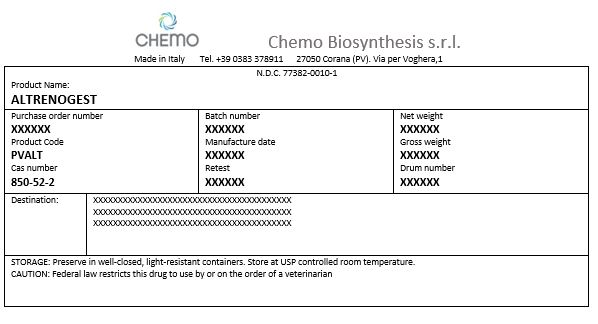 DRUG LABEL: Altrenogest
NDC: 77382-0010 | Form: POWDER
Manufacturer: Chemo Biosynthesis s.r.l.
Category: other | Type: BULK INGREDIENT - ANIMAL DRUG
Date: 20220615

ACTIVE INGREDIENTS: ALTRENOGEST 1 kg/1 kg

PACKAGE LABEL

Altrenogest